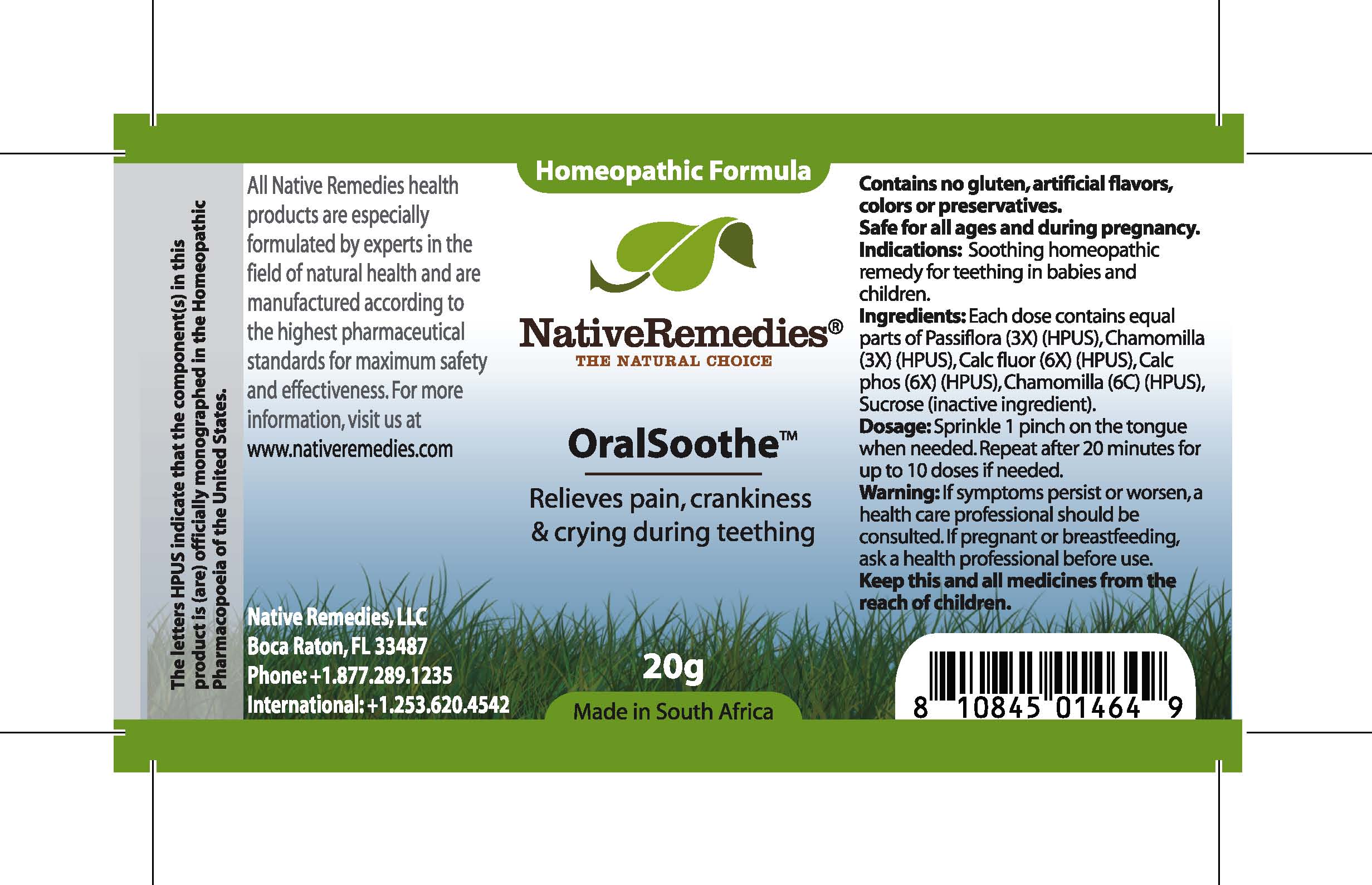 DRUG LABEL: Oral Soothe
NDC: 68647-165 | Form: GRANULE
Manufacturer: Feelgood Health
Category: homeopathic | Type: HUMAN OTC DRUG LABEL
Date: 20100827

ACTIVE INGREDIENTS: PASSIFLORA INCARNATA TOP 3 [hp_X]/40 mg; MATRICARIA RECUTITA 3 [hp_X]/40 mg; CALCIUM FLUORIDE 6 [hp_X]/40 mg; ANHYDROUS DIBASIC CALCIUM PHOSPHATE 6 [hp_X]/40 mg; MATRICARIA RECUTITA 6 [hp_C]/40 mg
INACTIVE INGREDIENTS: SUCROSE 20000 mg/20000 mg

ORALSOOTHE

PURPOSE

Relieves pain, crankiness and crying during teething

INDICATIONS AND USAGE

Indications: Soothing homeopathic remedy for teething in babies and children.

DOSAGE AND ADMINISTRATION

Dosage: Sprinkle 1 pinch on the tongue when needed. Repeat after 20 minutes for up to 10 doses if needed.

GENERAL PRECAUTIONS

Caution: If symptoms persist or worsen, a health care professional should be consulted. Keep this and all medicines from the reach of children.

ACTIVE INGREDIENT

Ingredients: Each dose contains equal parts of Passiflora (3X) (HPUS), Chamomilla (3X) (HPUS), Calc fluor (6X) (HPUS), Calc phos (6X) (HPUS), Chamomilla (6C) (HPUS)

Sucrose (inactive ingredient).

WARNINGS

Contains no gluten, artificial flavors, colors or preservatives.Safe for all ages.

PATIENT COUNSELING INFORMATION

All Native Remedies health products are especially formulated by experts in the field of natural health and are manufactured according to the highest pharmaceutical standards for maximum safety and effectiveness. For more information, visit us at www.nativeremedies.com

Distributed by

Native Remedies, LLC

6531 Park of Commerce Blvd.

Suite 160

Boca Raton, FL 33487

Phone: 1.877.289.1235

International: + 1.561.999.8857

The letters HPUS indicate that the component(s) in this product is (are) officially monographed in the Homeopathic Pharmacopoeia of the United States.

KEEP OUT OF REACH OF CHILDREN

Keep this and all medicines from the reach of children.